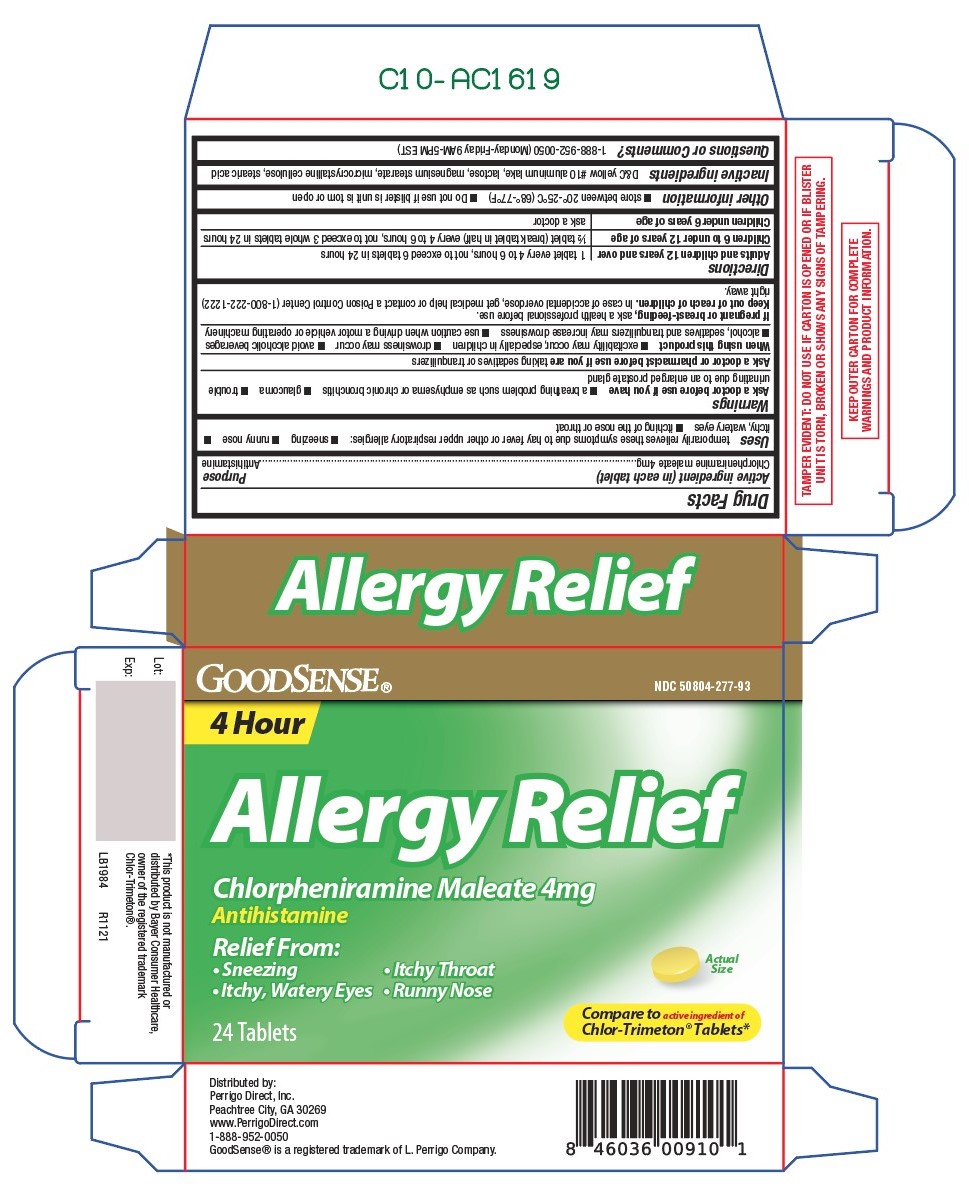 DRUG LABEL: Allergy Relief
NDC: 50804-277 | Form: TABLET
Manufacturer: Good Sense
Category: otc | Type: HUMAN OTC DRUG LABEL
Date: 20211130

ACTIVE INGREDIENTS: CHLORPHENIRAMINE MALEATE 4 mg/1 1
INACTIVE INGREDIENTS: D&C YELLOW NO. 10 ALUMINUM LAKE; LACTOSE, UNSPECIFIED FORM; MAGNESIUM STEARATE; MICROCRYSTALLINE CELLULOSE; STEARIC ACID

277 - Allergy Relief

Active ingredient(s)

Chlorpheniramine Maleate 4 mg

Purpose

Antihistamine

Use(s)

temporarily relieves these symptoms due to hay fever or other upper respiratory allergies:

- sneezing
- runny nose
- itchy, watery eyes
- itching of the nose or throat

Warnings

Ask a doctor before use if

- a breathing problem such as emphysema or chronic bronchitis
- glaucoma
- trouble urinating due to an enlarged prostate gland

Ask a doctor or pharmacist before use if

you are taking sedatives or tranquilizers

When using this product

- marked drowsiness may occur
- avoid alcoholic beverages
- alcohol, sedatives, and tranquilizers may increase drowsiness
- be careful when driving a motor vehicle or operating machinery
- excitability may occur especially in children

Pregnancy/Breastfeeding

If pregnant or breast-feeding, ask a health professional before use.

Keep out of reach of children

In case of accidental overdose, get medical help or contact a Poison Control Center (1-800-222-1222)
right away.

Directions

Adults and children 12 years and over: 1 tablet every 4 to 6 hours, not to exceed 6 tablets in 24 hours

Children 6 to under 12 years of age: ½ tablet (break tablet in half) every 4 to 6 hours, not to exceed 3 whole tablets in 24 hours

Children under 6 years of age: ask a doctor

Other information

- Store between 20°-25°C (68°-77°F)
- Do not use if blister is unit is torn or open

Inactive ingredients

D&C yellow #10 aluminum lake, lactose, magnesium stearate, microcrystalline cellulose, stearic acid

Questions

Questions or Comments? 1-888-952-0050 (Monday-Friday 9AM-5PM EST)

Principal Display Panel

Allergy Relief